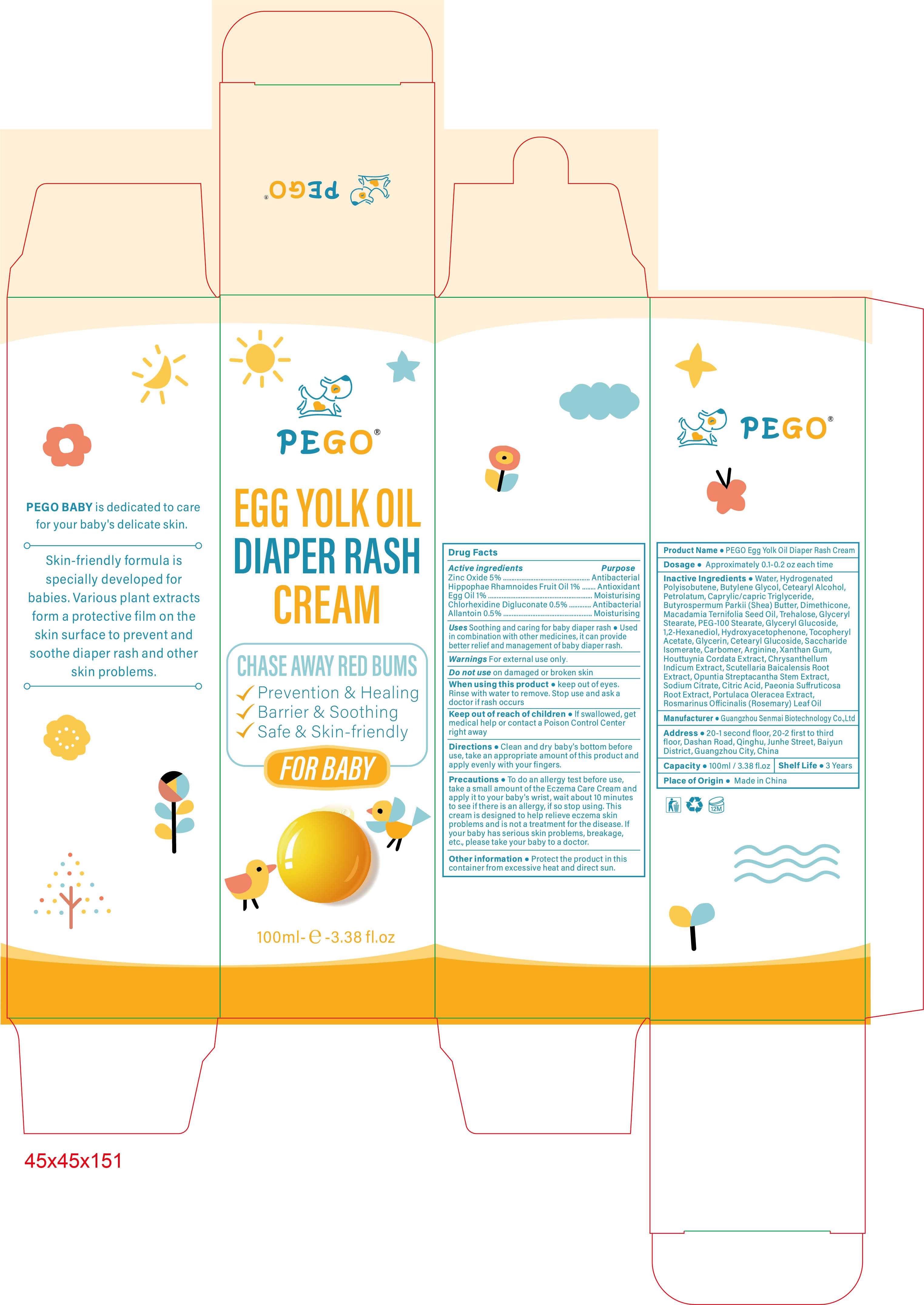 DRUG LABEL: PEGO Egg Yolk Oil Diaper Rash Cream
NDC: 84509-033 | Form: CREAM
Manufacturer: Guangzhou Senmai Biotechnology Co.,Ltd
Category: otc | Type: HUMAN OTC DRUG LABEL
Date: 20241022

ACTIVE INGREDIENTS: HIPPOPHAE RHAMNOIDES FRUIT OIL 1000 mg/100 mL; CHLORHEXIDINE 500 mg/100 mL; ZINC OXIDE 5000 mg/100 mL; EGG PHOSPHOLIPIDS 1000 mg/100 mL; ALLANTOIN 500 mg/100 mL
INACTIVE INGREDIENTS: GLYCERIN; ALPHA-TOCOPHEROL ACETATE; HOUTTUYNIA CORDATA EXTRACT; SCUTELLARIA BAICALENSIS ROOT; BUTYLENE GLYCOL; GLYCERYL GLUCOSIDE; HYDROXYACETOPHENONE; PAEONIA SUFFRUTICOSA ROOT BARK; TREHALOSE; GLYCERYL STEARATE; PURSLANE; SACCHARIDE ISOMERATE; CARBOMER; PETROLATUM; CAPRYLIC/CAPRIC TRIGLYCERIDE; OPUNTIA STREPTACANTHA STEM; WATER; CETEARYL ALCOHOL; ARGININE; ROSMARINUS OFFICINALIS (ROSEMARY) LEAF OIL; BUTYROSPERMUM PARKII (SHEA) BUTTER; CITRIC ACID; SODIUM CITRATE; XANTHAN GUM; CHRYSANTHELLUM INDICUM TOP; PEG-100 STEARATE; 1,2-HEXANEDIOL; CETEARYL GLUCOSIDE; HYDROGENATED POLYISOBUTENE (450 MW); DIMETHICONE; MACADAMIA TERNIFOLIA SEED OIL

Active Ingredients

Zinc Oxide 5%

Hippophae Rhamnoides Fruit Oil 1%

Egg Oil 1%

Chlorhexidine Digluconate 0.5%

Allantoin 0.5%

Purpose

Antibacterial

Antioxidant

Moisturising

Inactive Ingredients

Water, Hydrogenated Polyisobutene, Butylene Glycol, Cetearyl Alcohol, Petrolatum, Caprylic/capric Triglyceride, Butyrospermum Parkii (Shea) Butter, Dimethicone, Macadamia Ternifolia Seed Oil, Trehalose, Glyceryl Stearate, PEG-100 Stearate, Glyceryl Glucoside, 1,2-Hexanediol, Hydroxyacetophenone, Tocopheryl Acetate, Glycerin, Cetearyl Glucoside, Saccharide Isomerate, Carbomer, Arginine, Xanthan Gum, Houttuynia Cordata Extract, Chrysanthellum Indicum Extract, Scutellaria Baicalensis Root Extract, Opuntia Streptacantha Stem Extract, Sodium Citrate, Citric Acid, Paeonia Suffruticosa Root Extract, Portulaca Oleracea Extract, Rosmarinus Officinalis (Rosemary) Leaf Oil

DOSAGE

Approximately 0.1-0.2 oz each time

Warnings

Warnings For external use only.

Do not us

Do not use on damaged or broken skin

Keep out of reach of children

lf swallowed, get medical help or contact a Poison Control Center right away

When using this product

keep out of eyes. Rinse with water to remove. Stop use and ask a doctor if rash occurs

Precautions

To do an allergy test before use, take a small amount of the Eczema Care Cream and apply it to your baby's wrist, wait about 10 minutes to see if there is an allergy, if so stop using. This cream is designed to help relieve eczema skin problems and is not a treatment for the disease. If your baby has serious skin problems, breakage, etc., please take your baby to a doctor.

Product Name

PEGO Egg Yolk Oil Diaper Rash Cream

Manufacturer

Guangzhou Senmai Biotechnology Co.,Ltd

Address

20-1 second floor, 20-2 first to third floor, Dashan Road, Qinghu, Junhe Street, Baiyun District, Guangzhou City, China

Capacity

100ml / 3.38 fl.oz

Shelf Life

3 Years

Place of Origin

Made in China

Directions

Clean and dry baby's bottom before use, take an appropriate amount of this product and apply evenly with your fingers.

Other information

Protect the product in this container from excessive heat and direct sun.

Uses

Uses Soothing and caring for baby diaper rash ● Used in combination with other medicines, it can provide better relief and management of baby diaper rash.